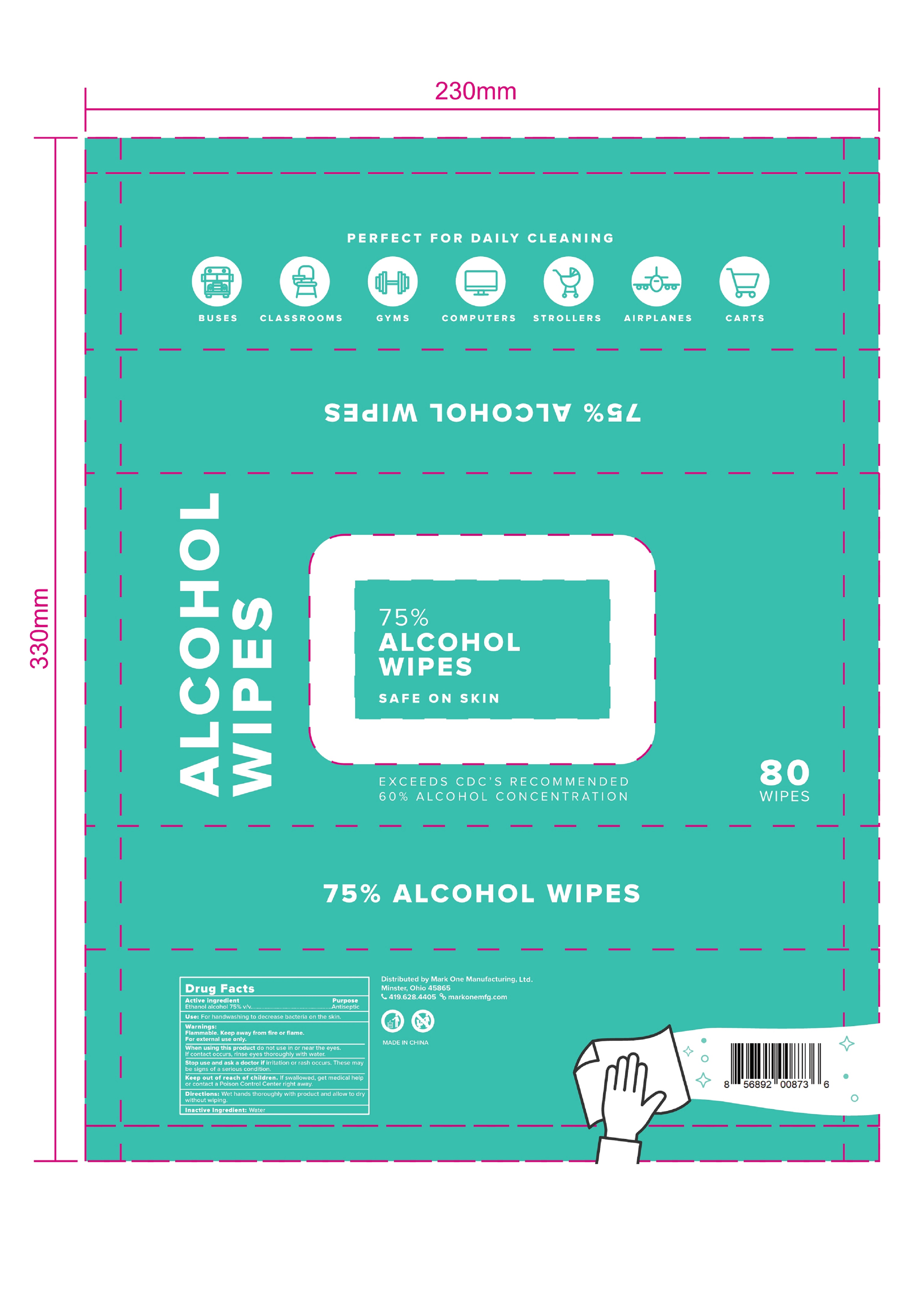 DRUG LABEL: ALCOHOL WIPES
NDC: 75163-005 | Form: CLOTH
Manufacturer: Zhuji Jianhe Paper Co., Ltd
Category: otc | Type: HUMAN OTC DRUG LABEL
Date: 20200920

ACTIVE INGREDIENTS: ALCOHOL 4.3 mL/1 1
INACTIVE INGREDIENTS: WATER

75163-005 80 CLOTH JIANHE 20200920

Active Ingredient(s)

Alcohol 75% v/v. Purpose: Antiseptic

Purpose

Antiseptic, 75% ALCOHOL WIPES

Use

For handwashing to decrease bacteria on the skin.

Warnings

Flammable. Keep away from fire or flame. For external use only.

When using this product do not in or near the eyes. If contact occurs, rinse eyes thoroughly with water.

Stop use and ask a doctor if irritation or rash occurs. These may be signs of a serious condition.

Keep out of reach of children. If swallowed, get medical help or contact a Poison Control Center right away.

Directions

- Directions Wet hands thoroughly with product and allow to dry without wiping.

Do not use

- In or near the eyes.
- On open skin wounds or burns.

Other information

- Avoid freezing and store below 110F (43C).
- Dispose the used wipe in trash, do not flush it into the toilet.
- May discolor certain fabrics or surfaces.

Inactive ingredients

Water

Package Label - Principal Display Panel

80 cloth in 1 BAG NDC: 75163-005-01